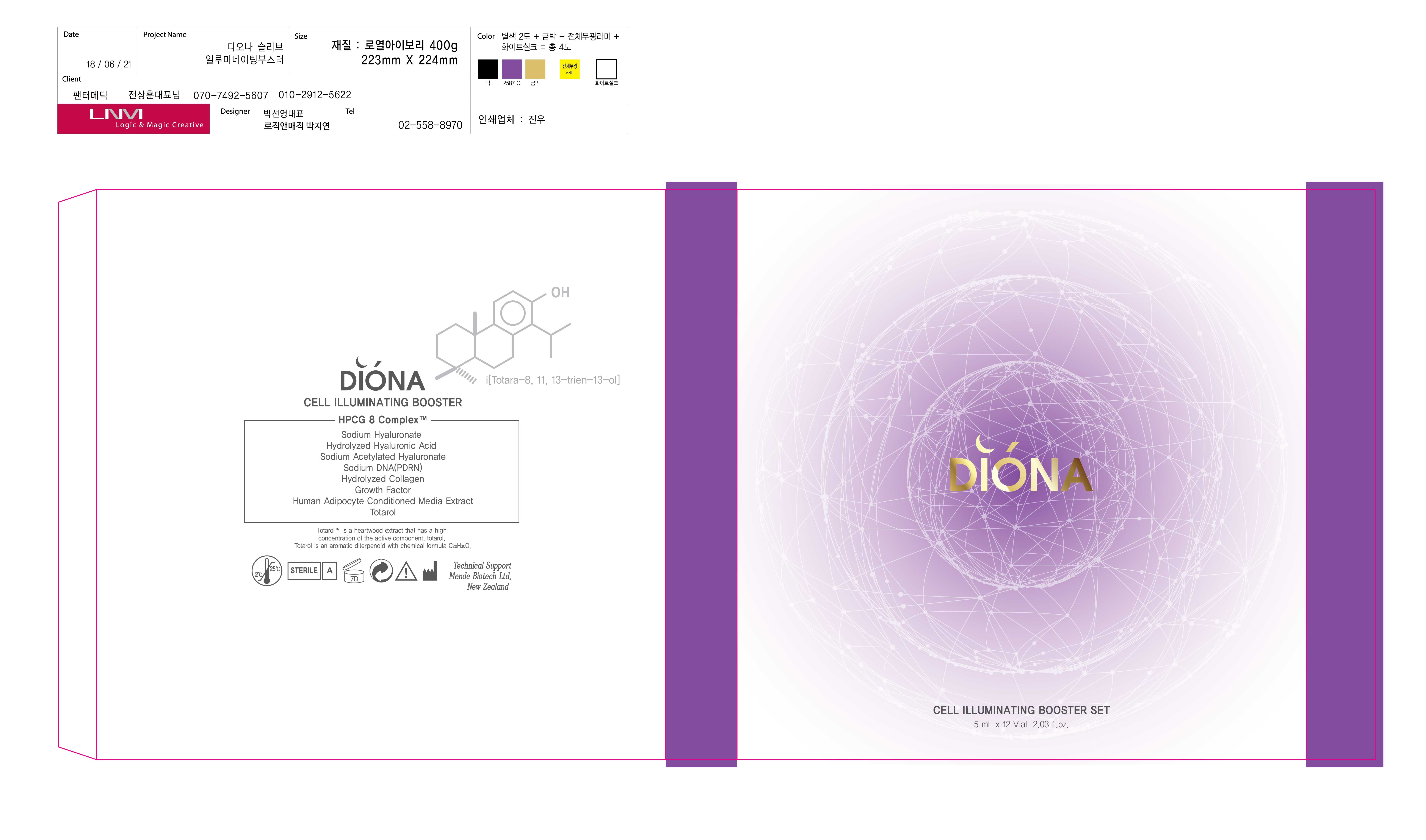 DRUG LABEL: DIONA CELL ILLUMINATING BOOSTER
NDC: 72573-0002 | Form: LIQUID
Manufacturer: VAATZ CO., LTD.
Category: otc | Type: HUMAN OTC DRUG LABEL
Date: 20180927

ACTIVE INGREDIENTS: GLYCERIN 0.877 g/100 mL
INACTIVE INGREDIENTS: WATER; BUTYLENE GLYCOL

Drug Facts

ACTIVE INGREDIENT

Glycerin

INACTIVE INGREDIENT

WATER, 1,2-HEXANEDIOL, NIACINAMIDE, SQUALANE, SODIUM DNA, ETC.

PURPOSE

Skin protectant

keep out of reach of the children

INDICATIONS AND USAGE

Apply an appropriate amount to skin and absorb it.

WARNINGS

1) If following symptoms occur after product use, stop using immediately and consult with a specialist: red spots, swelling, itchiness, and other skin irritations. 2) Avoid contact with eyes and open wounds. 3) Keep out of reach of children. 4) Do not store at high/low temperature. 5) Avoid direct sunlight.

DOSAGE AND ADMINISTRATION

for external use only